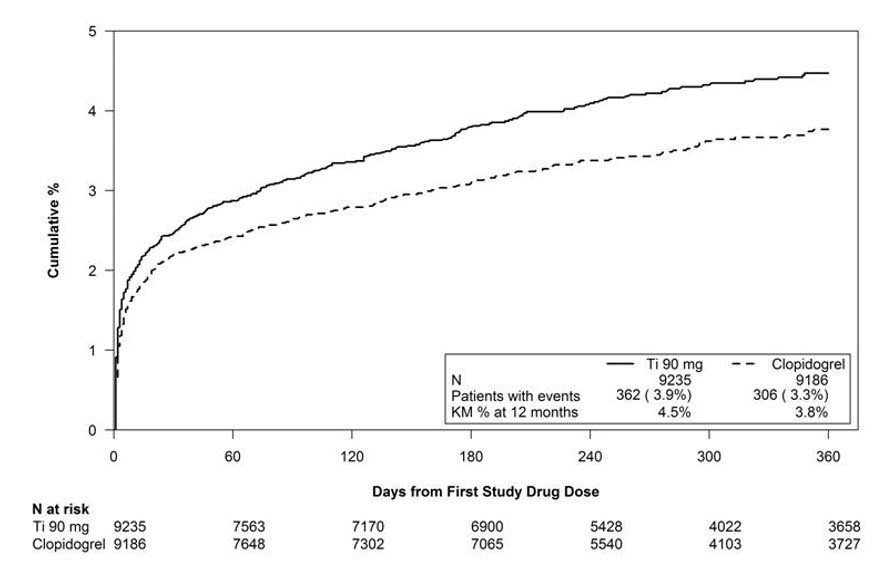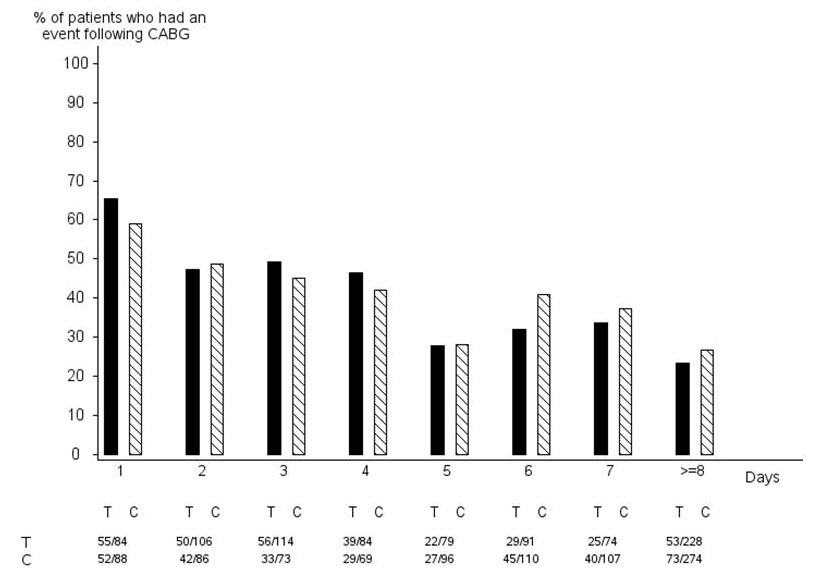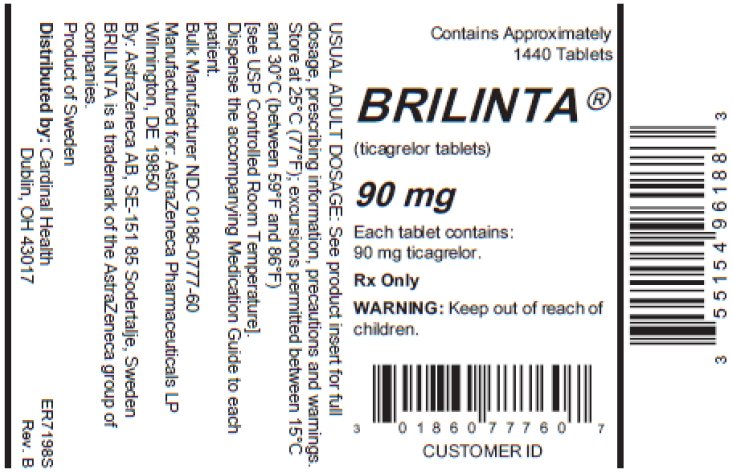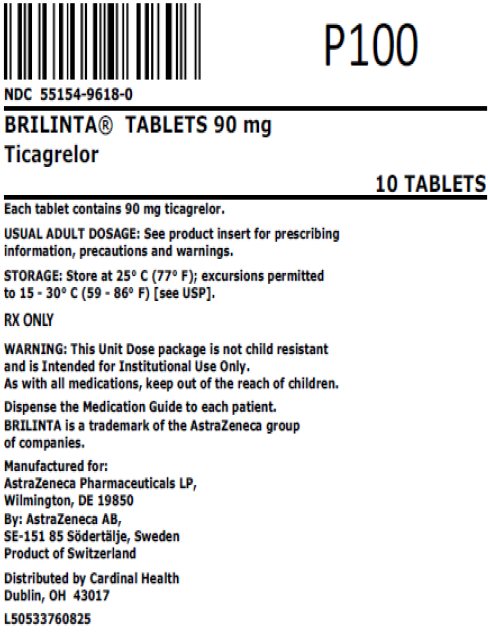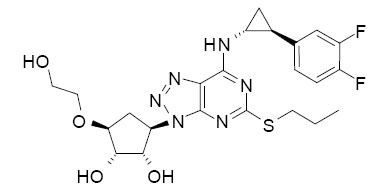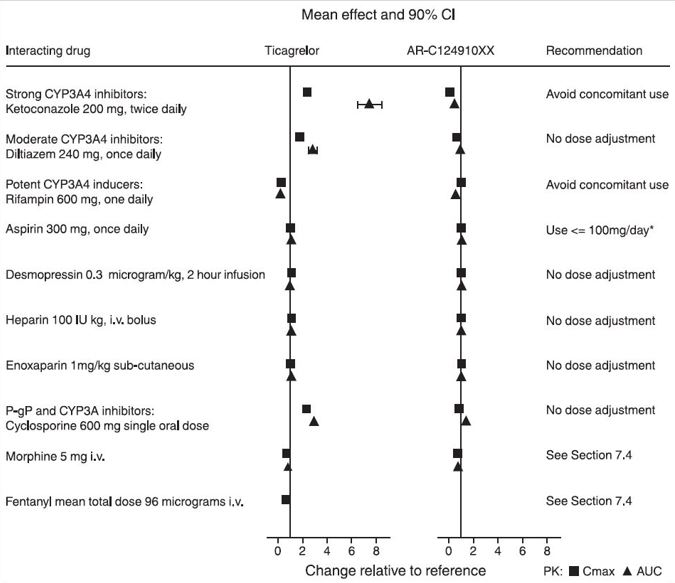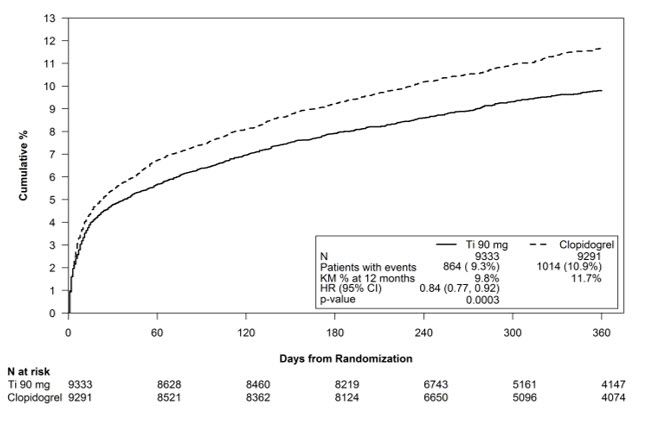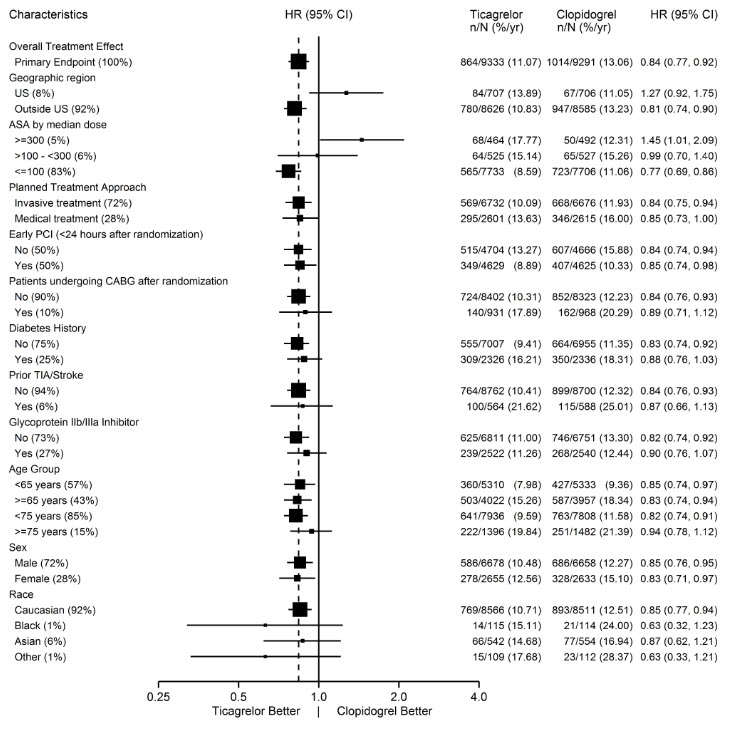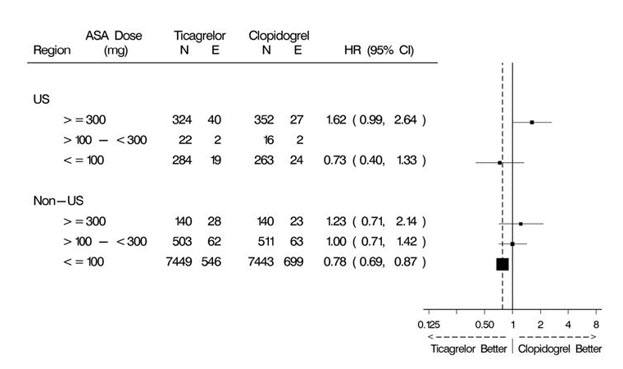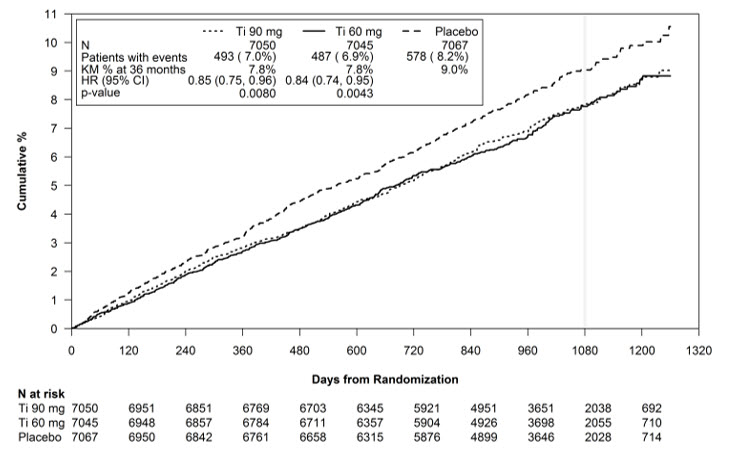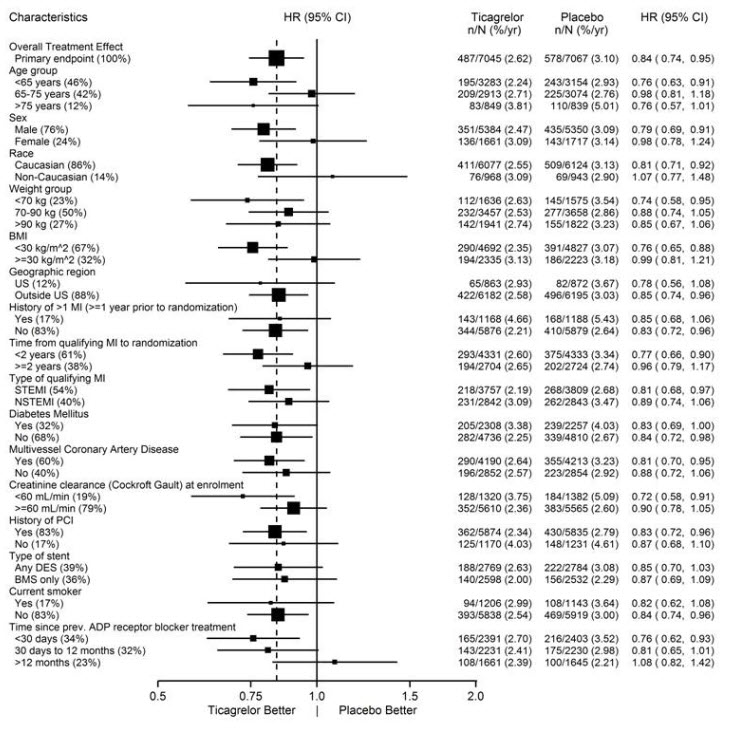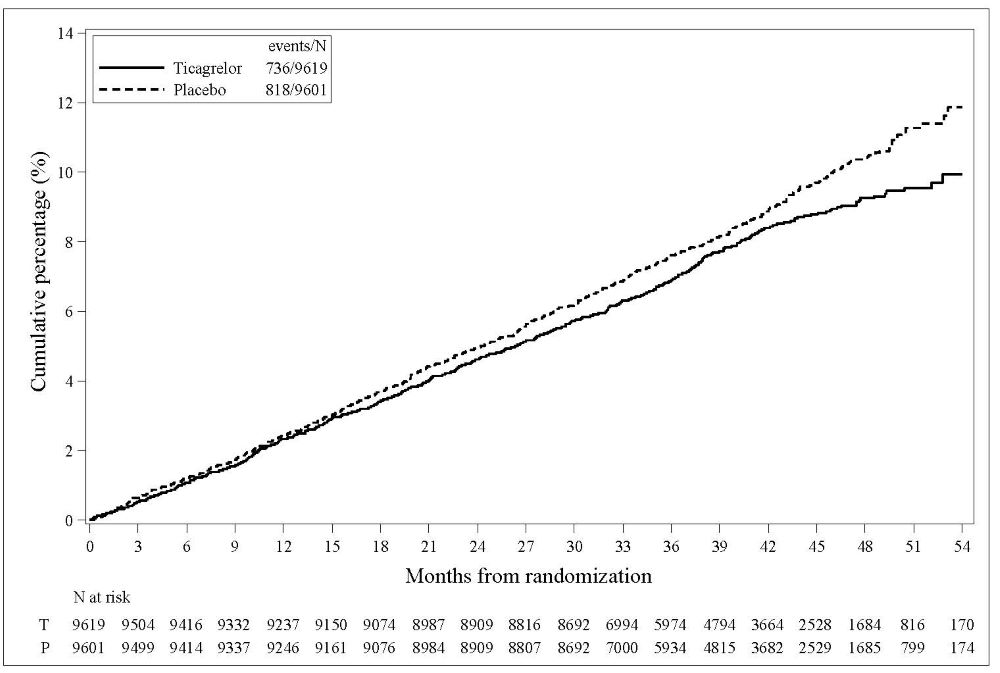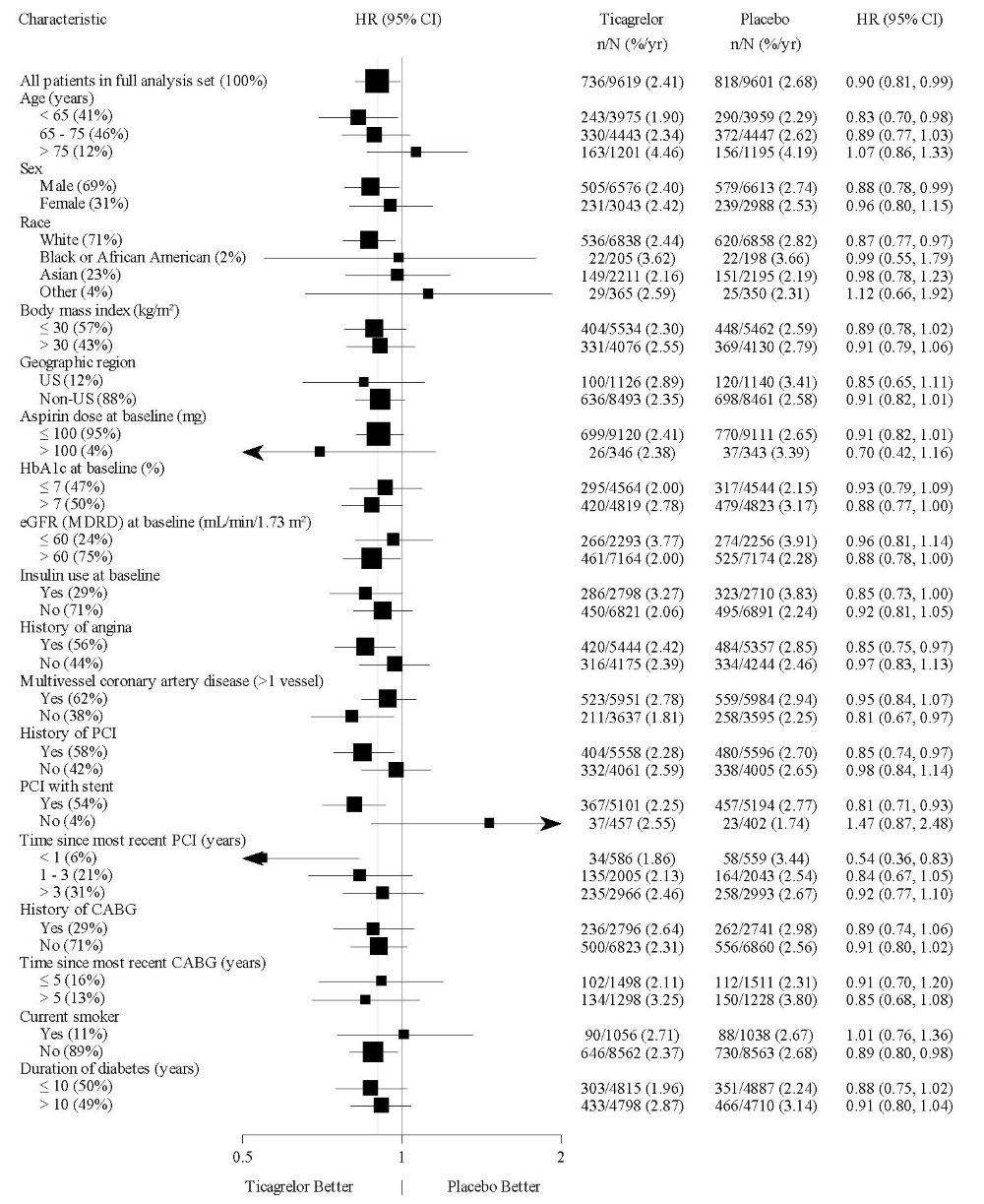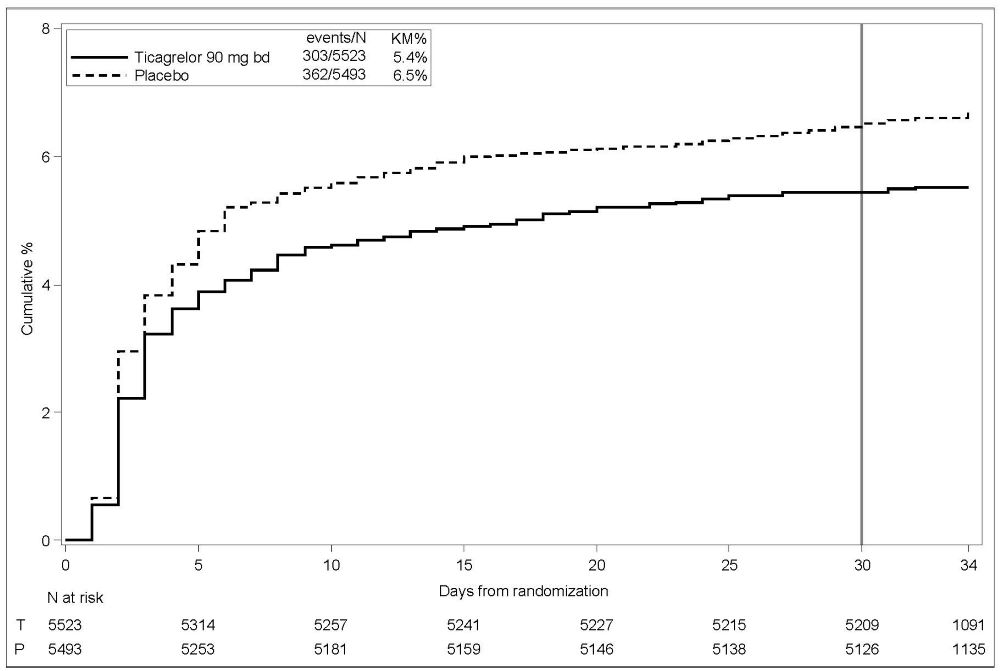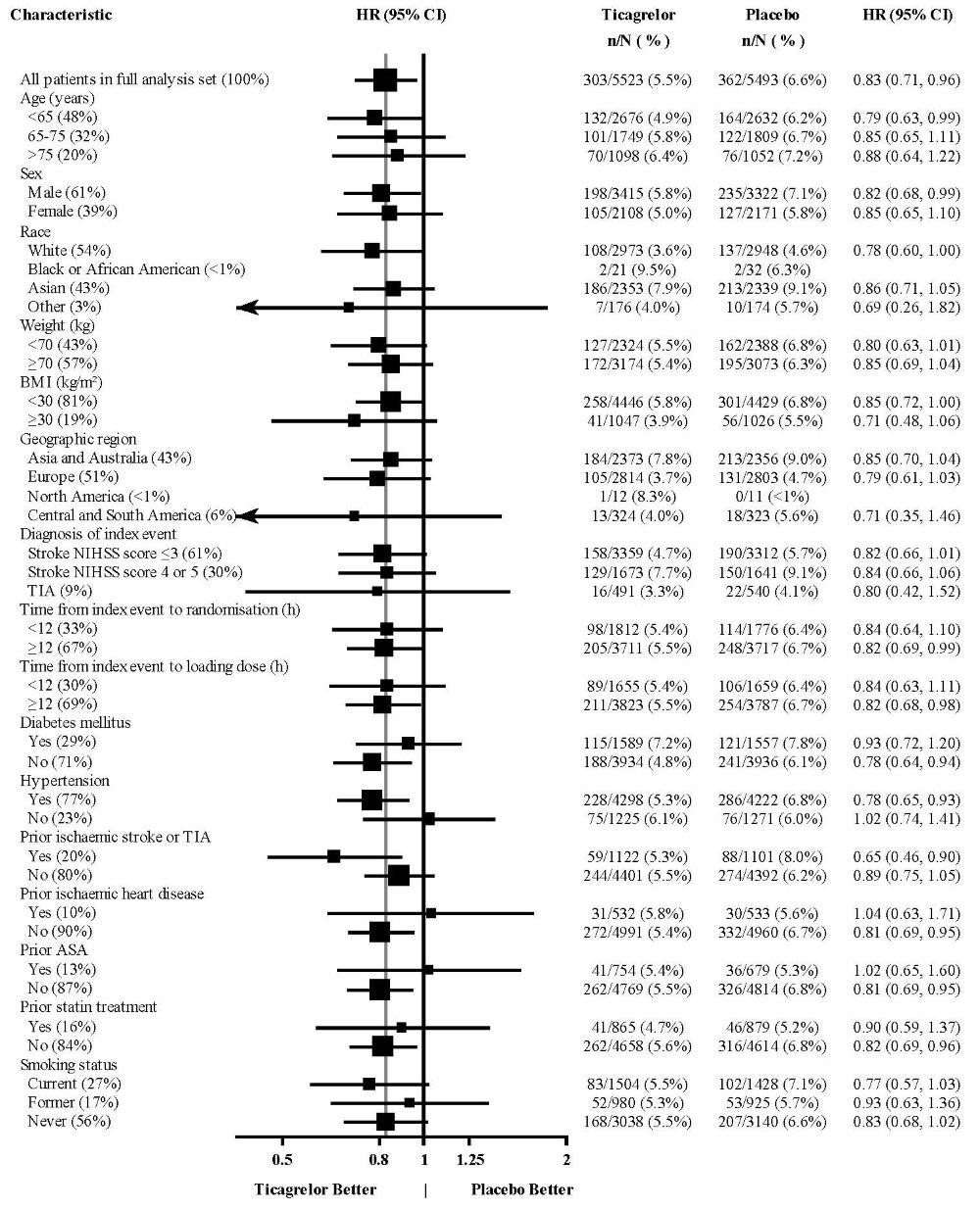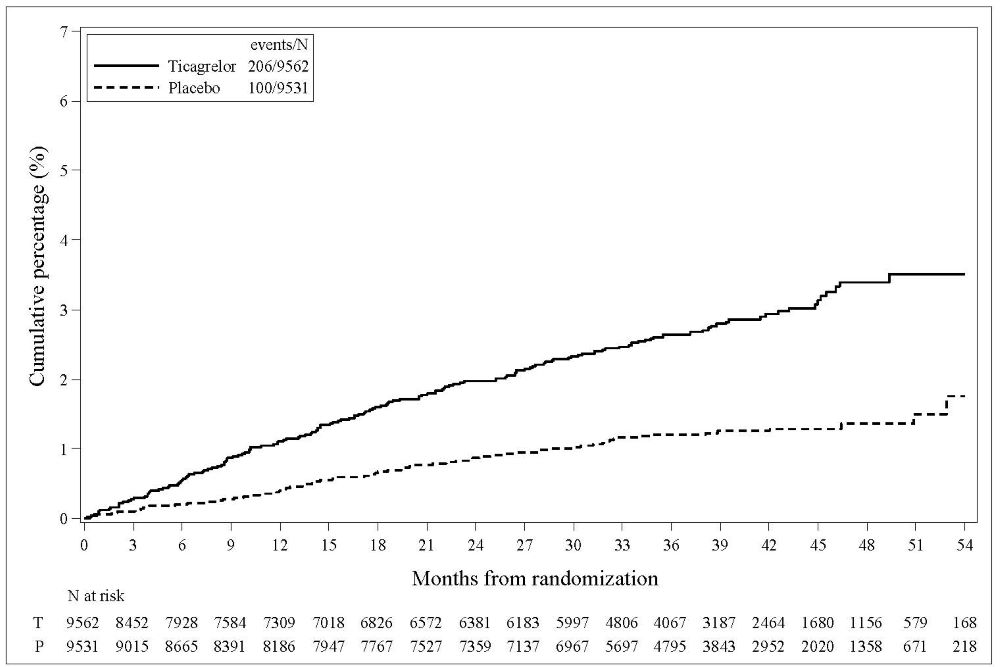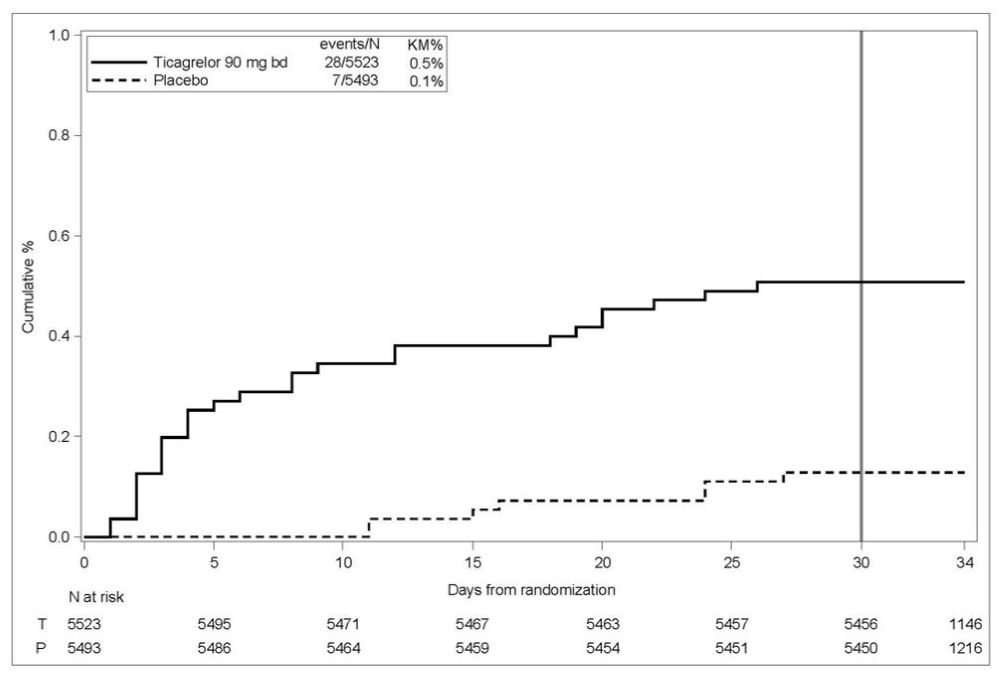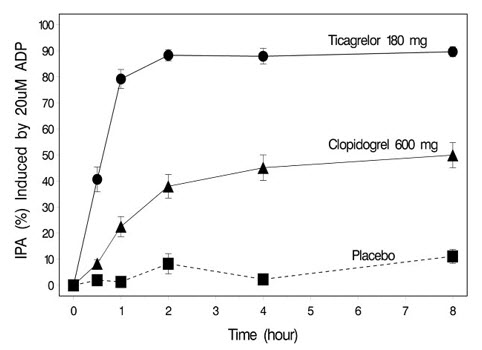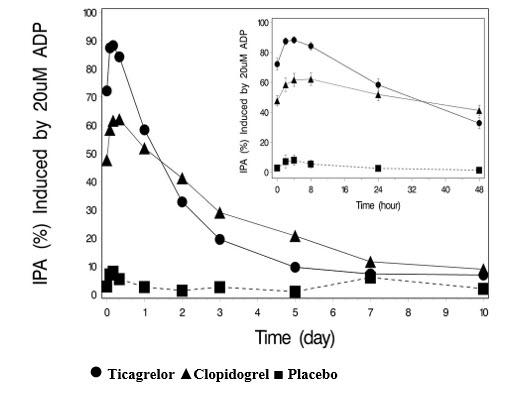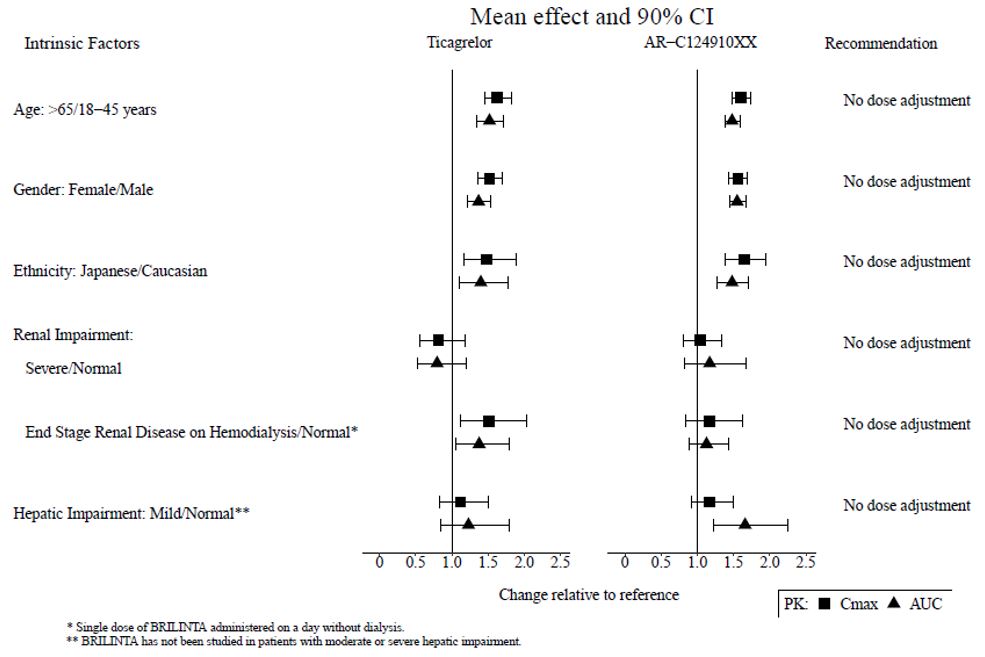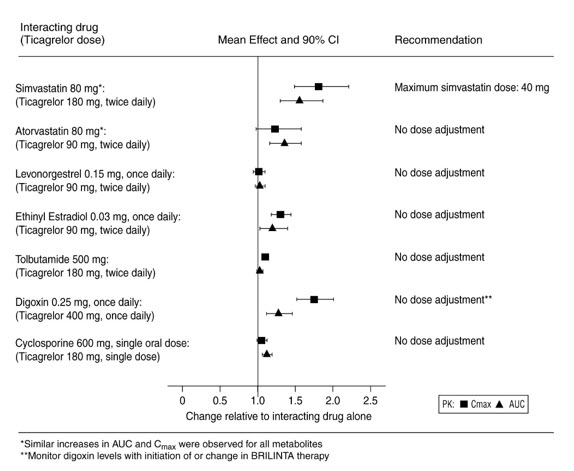 DRUG LABEL: BRILINTA
NDC: 55154-9618 | Form: TABLET
Manufacturer: Cardinal Health 107, LLC
Category: prescription | Type: HUMAN PRESCRIPTION DRUG LABEL
Date: 20260127

ACTIVE INGREDIENTS: TICAGRELOR 90 mg/1 1
INACTIVE INGREDIENTS: MANNITOL; DIBASIC CALCIUM PHOSPHATE DIHYDRATE; SODIUM STARCH GLYCOLATE TYPE A POTATO; HYDROXYPROPYL CELLULOSE (1600000 WAMW); MAGNESIUM STEARATE; HYPROMELLOSE, UNSPECIFIED; TITANIUM DIOXIDE; TALC; POLYETHYLENE GLYCOL 400; FERRIC OXIDE YELLOW

HIGHLIGHTS OF PRESCRIBING INFORMATION

These highlights do not include all the information needed to use BRILINTA safely and effectively. See full prescribing information for BRILINTA.
BRILINTA® (ticagrelor) tablets, for oral use
Initial U.S. Approval: 2011

RECENT MAJOR CHANGES

Dosage and Administration (2.2, 2.4) 03/2024

WARNING: BLEEDING RISK

See full prescribing information for complete boxed warning.

- BRILINTA, like other antiplatelet agents, can cause significant,
- sometimes fatal bleeding. (5.1, 6.1)
- Do not use BRILINTA in patients with active pathological
- bleeding or a history of intracranial hemorrhage. (4.1, 4.2)
- Do not start BRILINTA in patients undergoing urgent coronary
- artery bypass graft surgery (CABG). (5.1, 6.1)
- If possible, manage bleeding without discontinuing BRILINTA.
- Stopping BRILINTA increases the risk of subsequent
- cardiovascular events. (5.2)

1 INDICATIONS AND USAGE

BRILINTA is a P2Y12 platelet inhibitor indicated

- to reduce the risk of cardiovascular (CV) death, myocardial infarction (MI), and stroke in patients with acute coronary syndrome (ACS) or a history of MI. For at least the first 12 months following ACS, it is superior to clopidogrel.
  BRILINTA also reduces the risk of stent thrombosis in patients who have been stented for treatment of ACS. (1.1)
- to reduce the risk of a first MI or stroke in patients with coronary artery disease (CAD) at high risk for such events. While use is not limited to this setting, the efficacy of BRILINTA was established in a population with type 2 diabetes mellitus (T2DM). (1.2)
- to reduce the risk of stroke in patients with acute ischemic stroke (NIH Stroke Scale score ≤5) or high-risk transient ischemic attack (TIA). (1.3)

2 DOSAGE AND ADMINISTRATION

- ACS or History of MI
- Initiate treatment with 180 mg oral loading dose of BRILINTA. Then administer 90 mg twice daily during the first year. After one year, administer 60 mg twice daily. (2.2)
- Patients with CAD and No Prior Stroke or MI
- Administer 60 mg BRILINTA twice daily. (2.3)
- Acute Ischemic Stroke
- Initiate treatment with a 180 mg loading dose of BRILINTA then continue with 90 mg twice daily for up to 30 days. (2.4)

Use BRILINTA with a daily maintenance dose of aspirin of 75-100 mg. (2) However, in patients who have undergone PCI, consider single antiplatelet therapy with BRILINTA based on the evolving risk for thrombotic versus bleeding events. (2.2)

3 DOSAGE FORMS AND STRENGTHS

- 60 mg and 90 mg tablets (3)

4 CONTRAINDICATIONS

- History of intracranial hemorrhage. (4.1)
- Active pathological bleeding. (4.2)
- Hypersensitivity to ticagrelor or any component of the product. (4.3)

5 WARNINGS AND PRECAUTIONS

- Dyspnea was reported more frequently with BRILINTA than with control agents in clinical trials. Dyspnea from BRILINTA is self-limiting. (5.3)
- Severe Hepatic Impairment: Likely increase in exposure to ticagrelor. (5.6)
- Laboratory Test Interference: False negative platelet functional test results have been reported for Heparin Induced Thrombocytopenia (HIT). BRILINTA is not expected to impact PF4 antibody testing for HIT. (5.8)

6 ADVERSE REACTIONS

Most common adverse reactions (>5%) are bleeding and dyspnea. (5.1, 5.3, 6.1)

To report SUSPECTED ADVERSE REACTIONS, contact AstraZeneca at 1-800-236-9933 or FDA at 1-800-FDA-1088 or www.fda.gov/medwatch.

7 DRUG INTERACTIONS

- Avoid use with strong CYP3A inhibitors or CYP3A inducers. (7.1, 7.2)
- Opioids: Decreased exposure to ticagrelor. Consider use of parenteral anti-platelet agent. (7.3)
- Patients receiving more than 40 mg per day of simvastatin or lovastatin may be at increased risk of statin-related adverse effects. (7.4)
- Rosuvastatin plasma concentrations may increase. Monitor for statin-related adverse effects. (7.4)
- Monitor digoxin levels with initiation of or any change in BRILINTA. (7.5)

8 USE IN SPECIFIC POPULATIONS

- Lactation: Breastfeeding not recommended. (8.2)

FULL PRESCRIBING INFORMATION

WARNING: BLEEDING RISK

- BRILINTA, like other antiplatelet agents, can cause significant, sometimes fatal bleeding (5.1, 6.1).
- Do not use BRILINTA in patients with active pathological bleeding or a history of intracranial hemorrhage
- (4.1, 4.2).
- Do not start BRILINTA in patients undergoing urgent coronary artery bypass graft surgery (CABG) (5.1,
- 6.1).
- If possible, manage bleeding without discontinuing BRILINTA. Stopping BRILINTA increases the risk of
- subsequent cardiovascular events (5.2).

1 INDICATIONS AND USAGE

1.1 Acute Coronary Syndrome or a History of Myocardial Infarction

BRILINTA is indicated to reduce the risk of cardiovascular (CV) death, myocardial infarction (MI), and stroke in patients with acute coronary syndrome (ACS) or a history of MI. For at least the first 12 months following ACS, it is superior to clopidogrel.

BRILINTA also reduces the risk of stent thrombosis in patients who have been stented for treatment of ACS [see Clinical Studies (14.1)].

1.2 Coronary Artery Disease but No Prior Stroke or Myocardial Infarction

BRILINTA is indicated to reduce the risk of a first MI or stroke in patients with coronary artery disease (CAD) at high risk for such events [see Clinical Studies (14.2)]. While use is not limited to this setting, the efficacy of BRILINTA was established in a population with type 2 diabetes mellitus (T2DM).

1.3 Acute Ischemic Stroke or Transient Ischemic Attack (TIA)

BRILINTA is indicated to reduce the risk of stroke in patients with acute ischemic stroke (NIH Stroke Scale score ≤5) or high-risk transient ischemic attack (TIA) [see Clinical Studies (14.3)].

2 DOSAGE AND ADMINISTRATION

2.1 General Instructions

Advise patients who miss a dose of BRILINTA to take their next dose at its scheduled time.

For patients who are unable to swallow tablets whole, BRILINTA tablets can be crushed, mixed with water, and drunk.

The mixture can also be administered via a nasogastric tube (CH8 or greater) [see Clinical Pharmacology (12.3)].

Do not administer BRILINTA with another oral P2Y12 platelet inhibitor.

Avoid aspirin at doses higher than recommended [see Clinical Studies (14.1)].

2.2 Acute Coronary Syndrome or a History of Myocardial Infarction

Initiate treatment with a 180 mg loading dose of BRILINTA. Administer the first 90 mg maintenance dose of

BRILINTA, 6 to 12 hours after the loading dose. Administer 90 mg of BRILINTA twice daily during the first year after

an ACS event. After one year, administer 60 mg of BRILINTA twice daily.

Initiate BRILINTA with a daily maintenance dose of aspirin of 75 mg to 100 mg. However, in patients who have

undergone percutaneous coronary intervention (PCI), consider single antiplatelet therapy with BRILINTA based on the

evolving risk for thrombotic versus bleeding events [see Warnings and Precautions (5.1) and Clinical Studies (14)].

2.3 Coronary Artery Disease but No Prior Stroke or Myocardial Infarction

Administer 60 mg of BRILINTA twice daily.

Generally, use BRILINTA with a daily maintenance dose of aspirin of 75 mg to 100 mg [see Clinical Studies (14)].

2.4 Acute Ischemic Stroke or Transient Ischemic Attack (TIA)

Initiate treatment with a 180 mg loading dose of BRILINTA and then continue with 90 mg twice daily for up to 30 days.

Administer the first maintenance dose 6 to 12 hours after the loading dose.

Use BRILINTA with a loading dose of aspirin (300 mg to 325 mg) and a daily maintenance dose of aspirin of 75 mg to

100 mg [see Clinical Studies (14)].

3 DOSAGE FORMS AND STRENGTHS

BRILINTA (ticagrelor) 90 mg is supplied as a round, biconvex, yellow, film-coated tablet marked with a “90” above “T” on one side.

BRILINTA (ticagrelor) 60 mg is supplied as a round, biconvex, pink, film-coated tablet marked with “60” above “T” on one side.

4 CONTRAINDICATIONS

4.1 History of Intracranial Hemorrhage

BRILINTA is contraindicated in patients with a history of intracranial hemorrhage (ICH) because of a high risk of recurrent ICH in this population [see Clinical Studies (14.1), (14.2)].

4.2 Active Bleeding

BRILINTA is contraindicated in patients with active pathological bleeding such as peptic ulcer or intracranial hemorrhage [see Warnings and Precautions (5.1) and Adverse Reactions (6.1)].

4.3 Hypersensitivity

BRILINTA is contraindicated in patients with hypersensitivity (e.g., angioedema) to ticagrelor or any component of the product.

5 WARNINGS AND PRECAUTIONS

5.1 Risk of Bleeding

Drugs that inhibit platelet function including BRILINTA increase the risk of bleeding [see Warnings and Precautions

(5.2) and Adverse Reactions (6.1)].

Patients treated for acute ischemic stroke or TIA

Patients at NIHSS >5 and patients receiving thrombolysis were excluded from THALES and use of BRILINTA in such patients is not recommended.

5.2 Discontinuation of BRILINTA in Patients Treated for Coronary Artery Disease

Discontinuation of BRILINTA will increase the risk of myocardial infarction, stroke, and death in patients being treated

for coronary artery disease. If BRILINTA must be temporarily discontinued (e.g., to treat bleeding or for significant

surgery), restart it as soon as possible. When possible, interrupt therapy with BRILINTA for five days prior to surgery that

has a major risk of bleeding. Resume BRILINTA as soon as hemostasis is achieved.

5.3 Dyspnea

In clinical trials, about 14% (PLATO and PEGASUS) to 21% (THEMIS) of patients treated with BRILINTA developed dyspnea. Dyspnea was usually mild to moderate in intensity and often resolved during continued treatment but led to study drug discontinuation in 0.9% (PLATO), 1.0% (THALES), 4.3% (PEGASUS), and 6.9% (THEMIS) of patients.

In a substudy of PLATO, 199 subjects underwent pulmonary function testing irrespective of whether they reported dyspnea. There was no indication of an adverse effect on pulmonary function assessed after one month or after at least 6 months of chronic treatment.

If a patient develops new, prolonged, or worsened dyspnea that is determined to be related to BRILINTA, no specific treatment is required; continue BRILINTA without interruption if possible. In the case of intolerable dyspnea requiring discontinuation of BRILINTA, consider prescribing another antiplatelet agent.

5.4 Bradyarrhythmias

BRILINTA can cause ventricular pauses [see Adverse Reactions (6.1)]. Bradyarrhythmias including AV block have been

reported in the postmarketing setting. Patients with a history of sick sinus syndrome, 2nd or 3rd degree AV block or

bradycardia-related syncope not protected by a pacemaker were excluded from clinical studies and may be at increased

risk of developing bradyarrhythmias with ticagrelor.

5.5 Severe Hepatic Impairment

Avoid use of BRILINTA in patients with severe hepatic impairment. Severe hepatic impairment is likely to increase

serum concentration of ticagrelor. There are no studies of BRILINTA patients with severe hepatic impairment [see

Clinical Pharmacology (12.3)].

5.6 Central Sleep Apnea

Central sleep apnea (CSA) including Cheyne-Stokes respiration (CSR) has been reported in the post-marketing setting in

patients taking ticagrelor, including recurrence or worsening of CSA/CSR following rechallenge. If central sleep apnea is

suspected, consider further clinical assessment.

5.7 Laboratory Test Interferences

False negative functional tests for Heparin Induced Thrombocytopenia (HIT)

BRILINTA has been reported to cause false negative results in platelet functional tests (including the heparin-induced

platelet aggregation (HIPA) assay) for patients with Heparin Induced Thrombocytopenia (HIT). This is related to

inhibition of the P2Y12-receptor on the healthy donor platelets in the test by ticagrelor in the affected patient’s

serum/plasma. Information on concomitant treatment with BRILINTA is required for interpretation of HIT functional

tests. Based on the mechanism of BRILINTA interference, BRILINTA is not expected to impact PF4 antibody testing for

HIT.

6 ADVERSE REACTIONS

The following adverse reactions are also discussed elsewhere in the labeling:

- Bleeding [see Warnings and Precautions (5.1)]
- Dyspnea [see Warnings and Precautions (5.3)]

6.1 Clinical Trials Experience

Because clinical trials are conducted under widely varying conditions, adverse reaction rates observed in the clinical trials of a drug cannot be directly compared to rates in the clinical trials of another drug and may not reflect the rates observed in practice.

BRILINTA has been evaluated for safety in more than 58,000 patients.

Bleeding in PLATO (Reduction in risk of thrombotic events in ACS)

Figure 1 is a plot of time to the first non-CABG major bleeding event.

Figure 1 - Kaplan-Meier estimate of time to first non-CABG PLATO-defined major bleeding event (PLATO)

Frequency of bleeding in PLATO is summarized in Tables 1 and 2. About half of the non-CABG major bleeding events were in the first 30 days.

Table 1 - Non-CABG related bleeds (PLATO)
 | BRILINTA [90 mg BID] N=9235 | Clopidogrel N=9186
 | n (%) patients; with event | n (%) patients; with event
PLATO Major + Minor | 713 (7.7) | 567 (6.2)
Major | 362 (3.9) | 306 (3.3)
Fatal/Life-threatening | 171 (1.9) | 151 (1.6)
Fatal | 15 (0.2) | 16 (0.2)
Intracranial hemorrhage (Fatal/Life-threatening) | 26 (0.3) | 15 (0.2)
PLATO Minor bleed: requires medical intervention to stop or treat bleeding.
PLATO Major bleed: any one of the following: fatal; intracranial; intrapericardial with cardiac tamponade; hypovolemic shock or severe hypotension requiring intervention; significantly disabling (e.g., intraocular with permanent vision loss); associated with a decrease in Hb of at least 3 g/dL (or a fall in hematocrit (Hct) of at least 9%); transfusion of 2 or more units.
PLATO Major bleed, fatal/life-threatening: any major bleed as described above and associated with a decrease in Hb of more than 5 g/dL (or a fall in hematocrit (Hct) of at least 15%); transfusion of 4 or more units.
Fatal: A bleeding event that directly led to death within 7 days.

No baseline demographic factor altered the relative risk of bleeding with BRILINTA compared to clopidogrel.

In PLATO, 1584 patients underwent CABG surgery. The percentages of those patients who bled are shown in Figure 2 and Table 2.

Figure 2 - ‘Major fatal/life-threatening’ CABG-related bleeding by days from last dose of study drug to CABG procedure (PLATO)

X-axis is days from last dose of study drug prior to CABG.

The PLATO protocol recommended a procedure for withholding study drug prior to CABG or other major surgery without unblinding. If surgery was elective or non-urgent, study drug was interrupted temporarily, as follows: If local practice was to allow antiplatelet effects to dissipate before surgery, capsules (blinded clopidogrel) were withheld 5 days before surgery and tablets (blinded ticagrelor) were withheld for a minimum of 24 hours and a maximum of 72 hours before surgery. If local practice was to perform surgery without waiting for dissipation of antiplatelet effects capsules and tablets were withheld 24 hours prior to surgery and use of aprotinin or other hemostatic agents was allowed. If local practice was to use IPA monitoring to determine when surgery could be performed both the capsules and tablets were withheld at the same time and the usual monitoring procedures followed.

T Ticagrelor; C Clopidogrel.

Table 2 - CABG-related bleeding (PLATO)
 | BRILINTA [90 mg BID]; N=770 | Clopidogrel; N=814
 | n (%) patients; with event | n (%) patients; with event
PLATO Total Major | 626 (81.3) | 666 (81.8)
Fatal/Life-threatening | 337 (43.8) | 350 (43.0)
Fatal | 6 (0.8) | 7 (0.9)
PLATO Major bleed: any one of the following: fatal; intracranial; intrapericardial with cardiac tamponade; hypovolemic shock or severe hypotension requiring intervention; significantly disabling (e.g., intraocular with permanent vision loss); associated with a decrease in Hb of at least 3 g/dL (or a fall in hematocrit (Hct) of at least 9%); transfusion of 2 or more units.
PLATO Major bleed, fatal/life-threatening: any major bleed as described above and associated with a decrease in Hb of more than 5 g/dL (or a fall in hematocrit (Hct) of at least 15%); transfusion of 4 or more units.

When antiplatelet therapy was stopped 5 days before CABG, major bleeding occurred in 75% of BRILINTA treated patients and 79% on clopidogrel.

Other Adverse Reactions in PLATO

Adverse reactions that occurred at a rate of 4% or more in PLATO are shown in Table 3.

Table 3 - Percentage of patients reporting non-hemorrhagic adverse reactions at least 4% or more in either group and more frequently on BRILINTA (PLATO)
 | BRILINTA [90 mg BID] N=9235 | Clopidogrel N=9186
Dyspnea | 13.8 | 7.8
Dizziness | 4.5 | 3.9
Nausea | 4.3 | 3.8

Bleeding in PEGASUS (Secondary Prevention in Patients with a History of Myocardial Infarction)

Overall outcome of bleeding events in the PEGASUS study are shown in Table 4.

Table 4 - Bleeding events (PEGASUS)
 | BRILINTA [60 mg BID]; N=6958 | Placebo; N=6996
 | Events / 1000 patient years | Events / 1000 patient years
TIMI Major | 8 | 3
Fatal | 1 | 1
Intracranial hemorrhage | 2 | 1
TIMI Major or Minor | 11 | 5
TIMI Major: Fatal bleeding, OR any intracranial bleeding, OR clinically overt signs of hemorrhage associated with a drop in hemoglobin (Hgb) of ≥5 g/dL, or a fall in hematocrit (Hct) of ≥15%.
Fatal: A bleeding event that directly led to death within 7 days.
TIMI Minor: Clinically apparent with 3-5 g/dL decrease in hemoglobin.

The bleeding profile of BRILINTA 60 mg compared to aspirin alone was consistent across multiple pre-defined subgroups (e.g., by age, gender, weight, race, geographic region, concurrent conditions, concomitant therapy, stent, and medical history) for TIMI Major and TIMI Major or Minor bleeding events.

Other Adverse Reactions in PEGASUS

Adverse reactions that occurred in PEGASUS at rates of 3% or more are shown in Table 5.

Table 5 - Non-hemorrhagic adverse reactions reported in >3.0% of patients in the ticagrelor 60 mg treatment group (PEGASUS)
 | BRILINTA [60 mg BID] N=6958 | Placebo N=6996
Dyspnea | 14.2% | 5.5%
Dizziness | 4.5% | 4.1%
Diarrhea | 3.3% | 2.5%

Bleeding in THEMIS (Prevention of major CV events in patients with CAD and Type 2 Diabetes Mellitus)

The Kaplan-Meier curve of time to first TIMI Major bleeding event is presented in Figure 3.

Figure 3 – Time to first TIMI Major bleeding event (THEMIS)

T = Ticagrelor; P = Placebo; N = Number of patients

The bleeding events in THEMIS are shown below in Table 6.

Table 6 – Bleeding events (THEMIS)
 | BRILINTA; N=9562 | Placebo; N=9531
 | Events / 1000 patient years | Events / 1000 patient years
TIMI Major | 9 | 4
TIMI Major or Minor | 12 | 5
TIMI Major or Minor or Requiring medical attention | 46 | 18
Fatal bleeding | 1 | 0
Intracranial hemorrhage | 3 | 2

Bleeding in THALES (Reduction in risk of stroke in patients with acute ischemic stroke or TIA)

The Kaplan-Meier curve of time course of GUSTO severe bleeding events is presented in Figure 4.

Figure 4 – Time course of GUSTO severe bleeding events

KM%: Kaplan-Meier percentage evaluated at Day 30; T = Ticagrelor; P = placebo; N = Number of patients

GUSTO Severe: Any one of the following: fatal bleeding, intracranial bleeding (excluding asymptomatic hemorrhagic transformations of ischemic brain infarctions and excluding microhemorrhages < 10 mm evident only on gradient-echo magnetic resonance imaging), bleeding that caused hemodynamic compromise requiring intervention (e.g., systolic blood pressure <90 mmg Hg that required blood or fluid replacement, or vasopressor/inotropic support, or surgical intervention).

Intracranial bleeding and fatal bleeding in THALES: In total, there were 21 intracranial hemorrhages (ICHs) for BRILINTA and 6 ICHs for placebo. Fatal bleedings, almost all ICH, occurred in 11 for BRILINTA and in 2 for placebo.

Bradycardia

In a Holter substudy of about 3000 patients in PLATO, more patients had ventricular pauses with BRILINTA (6.0%) than with clopidogrel (3.5%) in the acute phase; rates were 2.2% and 1.6%, respectively, after 1 month. PLATO, PEGASUS, THEMIS and THALES excluded patients at increased risk of bradycardic events (e.g., patients who have sick sinus syndrome, 2nd or 3rd degree AV block, or bradycardic-related syncope and not protected with a pacemaker).

Lab abnormalities

Serum Uric Acid:

In PLATO, serum uric acid levels increased approximately 0.6 mg/dL from baseline on BRILINTA 90 mg and approximately 0.2 mg/dL on clopidogrel. The difference disappeared within 30 days of discontinuing treatment. Reports of gout did not differ between treatment groups in PLATO (0.6% in each group).

In PEGASUS, serum uric acid levels increased approximately 0.2 mg/dL from baseline on BRILINTA 60 mg and no elevation was observed on aspirin alone. Gout occurred more commonly in patients on BRILINTA than in patients on aspirin alone (1.5%, 1.1%). Mean serum uric acid concentrations decreased after treatment was stopped.

Serum Creatinine:

In PLATO, a >50% increase in serum creatinine levels was observed in 7.4% of patients receiving BRILINTA 90 mg compared to 5.9% of patients receiving clopidogrel. The increases typically did not progress with ongoing treatment and often decreased with continued therapy. Evidence of reversibility upon discontinuation was observed even in those with the greatest on treatment increases. Treatment groups in PLATO did not differ for renal-related serious adverse events such as acute renal failure, chronic renal failure, toxic nephropathy, or oliguria.

In PEGASUS, serum creatinine concentration increased by >50% in approximately 4% of patients receiving BRILINTA 60 mg, similar to aspirin alone. The frequency of renal related adverse events was similar for ticagrelor and aspirin alone regardless of age and baseline renal function.

6.2 Postmarketing Experience

The following adverse reactions have been identified during post-approval use of BRILINTA. Because these reactions are reported voluntarily from a population of an unknown size, it is not always possible to reliably estimate their frequency or establish a causal relationship to drug exposure.

Blood and lymphatic system disorders: Thrombotic Thrombocytopenic Purpura (TTP) has been rarely reported with the use of BRILINTA. TTP is a serious condition which can occur after a brief exposure (<2 weeks) and requires prompt treatment.

Immune system disorders: Hypersensitivity reactions including angioedema [see Contraindications (4.3)].

Respiratory Disorders: Central sleep apnea, Cheyne-Stokes respiration

Skin and subcutaneous tissue disorders: Rash

7 DRUG INTERACTIONS

7.1 Strong CYP3A Inhibitors

Strong CYP3A inhibitors substantially increase ticagrelor exposure and so increase the risk of dyspnea, bleeding, and other adverse events. Avoid use of strong inhibitors of CYP3A (e.g., ketoconazole, itraconazole, voriconazole, clarithromycin, nefazodone, ritonavir, saquinavir, nelfinavir, indinavir, atazanavir and telithromycin) [see Clinical Pharmacology (12.3)].

7.2 Strong CYP3A Inducers

Strong CYP3A inducers substantially reduce ticagrelor exposure and so decrease the efficacy of ticagrelor. Avoid use with strong inducers of CYP3A (e.g., rifampin, phenytoin, carbamazepine and phenobarbital) [see Clinical Pharmacology (12.3)].

7.3 Opioids

As with other oral P2Y12 inhibitors, co-administration of opioid agonists delay and reduce the absorption of ticagrelor and its active metabolite presumably because of slowed gastric emptying [see Clinical Pharmacology (12.3)]. Consider the use of a parenteral anti-platelet agent in acute coronary syndrome patients requiring co-administration of morphine or other opioid agonists.

7.4 Simvastatin, Lovastatin, Rosuvastatin

BRILINTA increases serum concentrations of simvastatin and lovastatin because these drugs are metabolized by CYP3A4. Avoid simvastatin and lovastatin doses greater than 40 mg [see Clinical Pharmacology (12.3)].

Brilinta increases serum concentration of rosuvastatin because rosuvastatin is a BCRP substrate [see Clinical Pharmacology (12.3)].

7.5 Digoxin

BRILINTA inhibits the P-glycoprotein transporter; monitor digoxin levels with initiation of or change in BRILINTA therapy [see Clinical Pharmacology (12.3)].

8 USE IN SPECIFIC POPULATIONS

8.1 Pregnancy

Risk Summary

Available data from case reports with BRILINTA use in pregnant women have not identified a drug-associated risk of major birth defects, miscarriage, or adverse maternal or fetal outcomes. Ticagrelor given to pregnant rats and pregnant rabbits during organogenesis caused structural abnormalities in the offspring at maternal doses about 5 to 7 times the maximum recommended human dose (MRHD) based on body surface area. When ticagrelor was given to rats during late gestation and lactation, pup death and effects on pup growth were seen at approximately 10 times the MRHD (see Data).

The estimated background risk of major birth defects and miscarriage for the indicated population is unknown. All pregnancies have a background risk of birth defect, loss, or other adverse outcomes. In the U.S. general population, the estimated background risk of major birth defects and miscarriage in clinically recognized pregnancies is 2 to 4% and 15 to 20%, respectively.

Data

Animal Data

In reproductive toxicology studies, pregnant rats received ticagrelor during organogenesis at doses from 20 to 300 mg/kg/day. 20 mg/kg/day is approximately the same as the MRHD of 90 mg twice daily for a 60 kg human on a mg/m^2 basis. Adverse outcomes in offspring occurred at doses of 300 mg/kg/day (16.5 times the MRHD on a mg/m^2 basis) and included supernumerary liver lobe and ribs, incomplete ossification of sternebrae, displaced articulation of pelvis, and misshapen/misaligned sternebrae. At the mid-dose of 100 mg/kg/day (5.5 times the MRHD on a mg/m^2 basis), delayed development of liver and skeleton was seen. When pregnant rabbits received ticagrelor during organogenesis at doses from 21 to 63 mg/kg/day, fetuses exposed to the highest maternal dose of 63 mg/kg/day (6.8 times the MRHD on a mg/m^2 basis) had delayed gall bladder development and incomplete ossification of the hyoid, pubis and sternebrae occurred.

In a prenatal/postnatal study, pregnant rats received ticagrelor at doses of 10 to 180 mg/kg/day during late gestation and lactation. Pup death and effects on pup growth were observed at 180 mg/kg/day (approximately 10 times the MRHD on a mg/m^2 basis). Relatively minor effects such as delays in pinna unfolding and eye opening occurred at doses of 10 and 60 mg/kg (approximately one-half and 3.2 times the MRHD on a mg/m^2 basis).

8.2 Lactation

Risk Summary

There are no data on the presence of ticagrelor or its metabolites in human milk, the effects on the breastfed infant, or the effects on milk production. Ticagrelor and its metabolites were present in rat milk at higher concentrations than in maternal plasma. When a drug is present in animal milk, it is likely that the drug will be present in human milk. Breastfeeding is not recommended during treatment with BRILINTA.

8.4 Pediatric Use

The safety and effectiveness of BRILINTA have not been established in pediatric patients. Effectiveness was not demonstrated in an adequate and well-controlled study conducted in 101 BRILINTA-treated pediatric patients, aged 2 to <18 for reducing the rate of vaso-occlusive crises in sickle cell disease.

8.5 Geriatric Use

About half of the patients in PLATO, PEGASUS, THEMIS, and THALES were ≥65 years of age and at least 15% were ≥75 years of age. No overall differences in safety or effectiveness were observed between elderly and younger patients.

8.6 Hepatic Impairment

Ticagrelor is metabolized by the liver and impaired hepatic function can increase risks for bleeding and other adverse events. Avoid use of BRILINTA in patients with severe hepatic impairment. There is limited experience with BRILINTA in patients with moderate hepatic impairment; consider the risks and benefits of treatment, noting the probable increase in exposure to ticagrelor. No dosage adjustment is needed in patients with mild hepatic impairment [see Warnings and Precautions (5.5) and Clinical Pharmacology (12.3)].

8.7 Renal Impairment

No dosage adjustment is needed in patients with renal impairment [see Clinical Pharmacology (12.3)].

Patients with End-Stage Renal Disease on dialysis

Clinical efficacy and safety studies with BRILINTA did not enroll patients with end-stage renal disease (ESRD) on dialysis. In patients with ESRD maintained on intermittent hemodialysis, no clinically significant difference in concentrations of ticagrelor and its metabolite and platelet inhibition are expected compared to those observed in patients with normal renal function [see Clinical Pharmacology (12.3)]. It is not known whether these concentrations will lead to similar efficacy and safety in patients with ESRD on dialysis as were seen in PLATO, PEGASUS, THEMIS and THALES.

10 OVERDOSAGE

There is currently no known treatment to reverse the effects of BRILINTA, and ticagrelor is not dialyzable. Treatment of overdose should follow local standard medical practice. Bleeding is the expected pharmacologic effect of overdosing. If bleeding occurs, appropriate supportive measures should be taken.

Platelet transfusion did not reverse the antiplatelet effect of BRILINTA in healthy volunteers and is unlikely to be of clinical benefit in patients with bleeding.

Other effects of overdose may include gastrointestinal effects (nausea, vomiting, diarrhea) or ventricular pauses. Monitor the ECG.

11 DESCRIPTION

BRILINTA contains ticagrelor, a cyclopentyltriazolopyrimidine, inhibitor of platelet activation and aggregation mediated by the P2Y12 ADP-receptor. Chemically it is (1S,2S,3R,5S)-3-[7-{[(1R,2S)-2-(3,4-difluorophenyl)cyclopropyl]amino}-5-(propylthio)-3H-[1,2,3]-triazolo[4,5-d]pyrimidin-3-yl]-5-(2-hydroxyethoxy)cyclopentane-1,2-diol. The empirical formula of ticagrelor is C23H28F2N6O4S and its molecular weight is 522.57. The chemical structure of ticagrelor is:

Ticagrelor is a crystalline powder with an aqueous solubility of approximately 10 μg/mL at room temperature.

BRILINTA 90 mg tablets for oral administration contain 90 mg of ticagrelor and the following ingredients: mannitol, dibasic calcium phosphate, sodium starch glycolate, hydroxypropyl cellulose, magnesium stearate, hydroxypropyl methylcellulose, titanium dioxide, talc, polyethylene glycol 400, and ferric oxide yellow.

BRILINTA 60 mg tablets for oral administration contain 60 mg of ticagrelor and the following ingredients: mannitol, dibasic calcium phosphate, sodium starch glycolate, hydroxypropyl cellulose, magnesium stearate, hydroxypropyl methylcellulose, titanium dioxide, polyethylene glycol 400, ferric oxide black, and ferric oxide red.

12 CLINICAL PHARMACOLOGY

12.1 Mechanism of Action

Ticagrelor and its major metabolite reversibly interact with the platelet P2Y12 ADP-receptor to prevent signal transduction and platelet activation. Ticagrelor and its active metabolite are approximately equipotent.

12.2 Pharmacodynamics

The inhibition of platelet aggregation (IPA) by ticagrelor and clopidogrel was compared in a 6-week study examining both acute and chronic platelet inhibition effects in response to 20 μM ADP as the platelet aggregation agonist.

The onset of IPA was evaluated on Day 1 of the study following loading doses of 180 mg ticagrelor or 600 mg clopidogrel. As shown in Figure 5, IPA was higher in the ticagrelor group at all time points. The maximum IPA effect of ticagrelor was reached at around 2 hours, and was maintained for at least 8 hours.

The offset of IPA was examined after 6 weeks on ticagrelor 90 mg twice daily or clopidogrel 75 mg daily, again in response to 20 μM ADP.

As shown in Figure 6, mean maximum IPA following the last dose of ticagrelor was 88% and 62% for clopidogrel. The insert in Figure 6 shows that after 24 hours, IPA in the ticagrelor group (58%) was similar to IPA in clopidogrel group (52%), indicating that patients who miss a dose of ticagrelor would still maintain IPA similar to the trough IPA of patients treated with clopidogrel. After 5 days, IPA in the ticagrelor group was similar to IPA in the placebo group. It is not known how either bleeding risk or thrombotic risk track with IPA, for either ticagrelor or clopidogrel.

Figure 5 - Mean inhibition of platelet aggregation (±SE) following single oral doses of placebo, 180 mg ticagrelor or 600 mg clopidogrel

Figure 6 - Mean inhibition of platelet aggregation (IPA) following 6 weeks on placebo, ticagrelor 90 mg twice daily, or clopidogrel 75 mg daily

Transitioning from clopidogrel to BRILINTA resulted in an absolute IPA increase of 26.4% and from BRILINTA to clopidogrel resulted in an absolute IPA decrease of 24.5%. Patients can be transitioned from clopidogrel to BRILINTA without interruption of antiplatelet effect [see Dosage and Administration (2)].

12.3 Pharmacokinetics

Ticagrelor demonstrates dose proportional pharmacokinetics, which are similar in patients and healthy volunteers.

Absorption

BRILINTA can be taken with or without food. Absorption of ticagrelor occurs with a median tmax of 1.5 h (range 1.0–4.0). The formation of the major circulating metabolite AR-C124910XX (active) from ticagrelor occurs with a median tmax of 2.5 h (range 1.5-5.0).

The mean absolute bioavailability of ticagrelor is about 36% (range 30%-42%). Ingestion of a high-fat meal had no effect on ticagrelor Cmax, but resulted in a 21% increase in AUC. The Cmax of its major metabolite was decreased by 22% with no change in AUC.

BRILINTA as crushed tablets mixed in water, given orally or administered through a nasogastric tube into the stomach, is bioequivalent to whole tablets (AUC and Cmax within 80-125% for ticagrelor and AR-C124910XX) with a median tmax of 1.0 hour (range 1.0 – 4.0) for ticagrelor and 2.0 hours (range 1.0 –8.0) for AR-C124910XX.

Distribution

The steady state volume of distribution of ticagrelor is 88 L. Ticagrelor and the active metabolite are extensively bound to human plasma proteins (>99%).

Metabolism

CYP3A4 is the major enzyme responsible for ticagrelor metabolism and the formation of its major active metabolite. Ticagrelor and its major active metabolite are weak P-glycoprotein substrates and inhibitors. The systemic exposure to the active metabolite is approximately 30-40% of the exposure of ticagrelor. Ticagrelor is a BCRP inhibitor.

Excretion

The primary route of ticagrelor elimination is hepatic metabolism. When radiolabeled ticagrelor is administered, the mean recovery of radioactivity is approximately 84% (58% in feces, 26% in urine). Recoveries of ticagrelor and the active metabolite in urine were both less than 1% of the dose. The primary route of elimination for the major metabolite of ticagrelor is most likely to be biliary secretion. The mean t1/2 is approximately 7 hours for ticagrelor and 9 hours for the active metabolite.

Specific Populations

The effects of age, gender, ethnicity, renal impairment and mild hepatic impairment on the pharmacokinetics of ticagrelor are presented in Figure 7. Effects are modest and do not require dose adjustment.

Patients with End-Stage Renal Disease on Hemodialysis

In patients with end stage renal disease on hemodialysis AUC and Cmax of BRILINTA 90 mg administered on a day without dialysis were 38% and 51% higher respectively, compared to subjects with normal renal function. A similar increase in exposure was observed when BRILINTA was administered immediately prior to dialysis showing that BRILINTA is not dialyzable. Exposure of the active metabolite increased to a lesser extent. The IPA effect of BRILINTA was independent of dialysis in patients with end stage renal disease and similar to healthy adults with normal renal function.

Figure 7 - Impact of intrinsic factors on the pharmacokinetics of ticagrelor

Effects of Other Drugs on BRILINTA

CYP3A4 is the major enzyme responsible for ticagrelor metabolism and the formation of its major active metabolite. The effects of other drugs on the pharmacokinetics of ticagrelor are presented in Figure 8 as change relative to ticagrelor given alone (test/reference). Strong CYP3A inhibitors (e.g., ketoconazole, itraconazole, and clarithromycin) substantially increase ticagrelor exposure. Moderate CYP3A inhibitors have lesser effects (e.g., diltiazem). CYP3A inducers (e.g., rifampin) substantially reduce ticagrelor blood levels. P-gp inhibitors (e.g., cyclosporine) increase ticagrelor exposure.

Co-administration of 5 mg intravenous morphine with 180 mg loading dose of ticagrelor decreased observed mean ticagrelor exposure by up to 25% in healthy adults and up to 36% in ACS patients undergoing PCI. Tmax was delayed by 1-2 hours. Exposure of the active metabolite decreased to a similar extent. Morphine co-administration did not delay or decrease platelet inhibition in healthy adults. Mean platelet aggregation was higher up to 3 hours post loading dose in ACS patients co-administered with morphine.

Co-administration of intravenous fentanyl with 180 mg loading dose of ticagrelor in ACS patients undergoing PCI resulted in similar effects on ticagrelor exposure and platelet inhibition.

Figure 8 - Effect of co-administered drugs on the pharmacokinetics of ticagrelor

*See Dosage and Administration (2)

Effects of BRILINTA on Other Drugs

In vitro metabolism studies demonstrate that ticagrelor and its major active metabolite are weak inhibitors of CYP3A4, potential activators of CYP3A5 and inhibitors of the P-gp transporter. In vitro metabolism studies demonstrate that ticagrelor is a BCRP inhibitor. Ticagrelor and AR-C124910XX were shown to have no inhibitory effect on human CYP1A2, CYP2C19, and CYP2E1 activity. For specific in vivo effects on the pharmacokinetics of simvastatin, atorvastatin, ethinyl estradiol, levonorgesterol, tolbutamide, digoxin and cyclosporine, see Figure 9.

Figure 9 - Impact of BRILINTA on the pharmacokinetics of co-administered drugs

12.5 Pharmacogenomics

In a genetic substudy cohort of PLATO, the rate of thrombotic CV events in the BRILINTA arm did not depend on CYP2C19 loss of function status.

13 NONCLINICAL TOXICOLOGY

13.1 Carcinogenesis, Mutagenesis, Impairment of Fertility

Carcinogenesis

Ticagrelor was not carcinogenic in the mouse at doses up to 250 mg/kg/day or in the male rat at doses up to 120 mg/kg/day (19 and 15 times the MRHD of 90 mg twice daily on the basis of AUC, respectively). Uterine carcinomas, uterine adenocarcinomas and hepatocellular adenomas were seen in female rats at doses of 180 mg/kg/day (29‑fold the maximally recommended dose of 90 mg twice daily on the basis of AUC), whereas 60 mg/kg/day (8‑fold the MRHD based on AUC) was not carcinogenic in female rats.

Mutagenesis

Ticagrelor did not demonstrate genotoxicity when tested in the Ames bacterial mutagenicity test, mouse lymphoma assay and the rat micronucleus test. The active O-demethylated metabolite did not demonstrate genotoxicity in the Ames assay and mouse lymphoma assay.

Impairment of Fertility

Ticagrelor had no effect on male fertility at doses up to 180 mg/kg/day or on female fertility at doses up to 200 mg/kg/day (>15-fold the MRHD on the basis of AUC). Doses of ≥10 mg/kg/day given to female rats caused an increased incidence of irregular duration estrus cycles (1.5-fold the MRHD based on AUC).

14 CLINICAL STUDIES

14.1 Acute Coronary Syndromes and Secondary Prevention after Myocardial Infarction

PLATO

PLATO (NCT00391872) was a randomized double-blind study comparing BRILINTA (N=9333) to clopidogrel (N=9291), both given in combination with aspirin and other standard therapy, in patients with acute coronary syndromes (ACS), who presented within 24 hours of onset of the most recent episode of chest pain or symptoms. The study’s primary endpoint was the composite of first occurrence of cardiovascular death, non-fatal MI (excluding silent MI), or non-fatal stroke.

Patients who had already been treated with clopidogrel could be enrolled and randomized to either study treatment. Patients with previous intracranial hemorrhage, gastrointestinal bleeding within the past 6 months, or with known bleeding diathesis or coagulation disorder were excluded. Patients taking anticoagulants were excluded from participating and patients who developed an indication for anticoagulation during the trial were discontinued from study drug. Patients could be included whether there was intent to manage the ACS medically or invasively, but patient randomization was not stratified by this intent.

All patients randomized to BRILINTA received a loading dose of 180 mg followed by a maintenance dose of 90 mg twice daily. Patients in the clopidogrel arm were treated with an initial loading dose of clopidogrel 300 mg, if clopidogrel therapy had not already been given. Patients undergoing PCI could receive an additional 300 mg of clopidogrel at investigator discretion. A daily maintenance dose of aspirin 75-100 mg was recommended, but higher maintenance doses of aspirin were allowed according to local judgment. Patients were treated for at least 6 months and for up to 12 months.

PLATO patients were predominantly male (72%) and Caucasian (92%). About 43% of patients were >65 years and 15% were >75 years. Median exposure to study drug was 276 days. About half of the patients received pre-study clopidogrel and about 99% of the patients received aspirin at some time during PLATO. About 35% of patients were receiving a statin at baseline and 93% received a statin sometime during PLATO.

Table 7 shows the study results for the primary composite endpoint and the contribution of each component to the primary endpoint. Separate secondary endpoint analyses are shown for the overall occurrence of CV death, MI, and stroke and overall mortality.

Table 7 - Patients with outcome events (PLATO)
 | BRILINTA [Dosed at 90 mg bid.]; N=9333 | Clopidogrel; N=9291 | Hazard Ratio; (95% CI) | p-value
 | Events / 1000 patient years | Events / 1000 patient years | Hazard Ratio; (95% CI) | p-value
Composite of CV death, MI, or stroke | 111 | 131 | 0.84 (0.77, 0.92) | 0.0003
CV death | 32 | 43 | 0.74
Non-fatal MI | 64 | 76 | 0.84
Non-fatal stroke | 15 | 12 | 1.24
Secondary endpoints [Note: rates of first events for the components CV Death, MI and Stroke are the actual rates for first events for each component and do not add up to the overall rate of events in the composite endpoint.]
CV death | 45 | 57 | 0.79 (0.69, 0.91) | 0.0013
MI [Including patients who could have had other non-fatal events or died.] | 65 | 76 | 0.84 (0.75, 0.95) | 0.0045
Stroke | 16 | 14 | 1.17 (0.91, 1.52) | 0.22
All-cause mortality | 51 | 65 | 0.78 (0.69, 0.89) | 0.0003

The Kaplan-Meier curve (Figure 10) shows time to first occurrence of the primary composite endpoint of CV death, non-fatal MI or non-fatal stroke in the overall study.

Figure 10 - Time to first occurrence of CV death, MI, or stroke (PLATO)

The curves separate by 30 days [relative risk reduction (RRR) 12%] and continue to diverge throughout the 12‑month treatment period (RRR 16%).

Among 11,289 patients with PCI receiving any stent during PLATO, there was a lower risk of stent thrombosis (1.3% for adjudicated “definite”) than with clopidogrel (1.9%) (HR 0.67, 95% CI 0.50-0.91; p=0.009). The results were similar for drug-eluting and bare metal stents.

A wide range of demographic, concurrent baseline medications, and other treatment differences were examined for their influence on outcome. Some of these are shown in Figure 11. Such analyses must be interpreted cautiously, as differences can reflect the play of chance among a large number of analyses. Most of the analyses show effects consistent with the overall results, but there are two exceptions: a finding of heterogeneity by region and a strong influence of the maintenance dose of aspirin. These are considered further below.

Most of the characteristics shown are baseline characteristics, but some reflect post-randomization determinations (e.g., aspirin maintenance dose, use of PCI).

Figure 11 – Subgroup analyses of (PLATO)

Note: The figure above presents effects in various subgroups most of which are baseline characteristics and most of which were pre-specified. The 95% confidence limits that are shown do not take into account how many comparisons were made, nor do they reflect the effect of a particular factor after adjustment for all other factors. Apparent homogeneity or heterogeneity among groups should not be over-interpreted.

Regional Differences

Results in the rest of the world compared to effects in North America (US and Canada) show a smaller effect in North America, numerically inferior to the control and driven by the US subset. The statistical test for the US/non-US comparison is statistically significant (p=0.009), and the same trend is present for both CV death and non-fatal MI. The individual results and nominal p-values, like all subset analyses, need cautious interpretation, and they could represent chance findings. The consistency of the differences in both the CV mortality and non-fatal MI components, however, supports the possibility that the finding is reliable.

A wide variety of baseline and procedural differences between the US and non-US (including intended invasive vs. planned medical management, use of GPIIb/IIIa inhibitors, use of drug eluting vs. bare-metal stents) were examined to see if they could account for regional differences, but with one exception, aspirin maintenance dose, these differences did not appear to lead to differences in outcome.

Aspirin Dose

The PLATO protocol left the choice of aspirin maintenance dose up to the investigator and use patterns were different in US sites from sites outside of the US. About 8% of non-US investigators administered aspirin doses above 100 mg, and about 2% administered doses above 300 mg. In the US, 57% of patients received doses above 100 mg and 54% received doses above 300 mg. Overall results favored BRILINTA when used with low maintenance doses (≤100 mg) of aspirin, and results analyzed by aspirin dose were similar in the US and elsewhere. Figure 10 shows overall results by median aspirin dose. Figure 12 shows results by region and dose.

Figure 12 – CV death, MI, stroke by maintenance aspirin dose in the US and outside the US (PLATO)

Like any unplanned subset analysis, especially one where the characteristic is not a true baseline characteristic (but may be determined by usual investigator practice), the above analyses must be treated with caution. It is notable, however, that aspirin dose predicts outcome in both regions with a similar pattern, and that the pattern is similar for the two major components of the primary endpoint, CV death and non-fatal MI.

Despite the need to treat such results cautiously, there appears to be good reason to restrict aspirin maintenance dosage accompanying ticagrelor to 100 mg. Higher doses do not have an established benefit in the ACS setting, and there is a strong suggestion that use of such doses reduces the effectiveness of BRILINTA.

PEGASUS

The PEGASUS TIMI-54 study (NCT01225562) was a 21,162-patient, randomized, double-blind, placebo-controlled, parallel-group study. Two doses of ticagrelor, either 90 mg twice daily or 60 mg twice daily, co-administered with 75-150 mg of aspirin, were compared to aspirin therapy alone in patients with history of MI. The primary endpoint was the composite of first occurrence of CV death, non-fatal MI and non-fatal stroke. CV death and all-cause mortality were assessed as secondary endpoints.

Patients were eligible to participate if they were ≥50 years old, with a history of MI 1 to 3 years prior to randomization, and had at least one of the following risk factors for thrombotic cardiovascular events: age ≥65 years, diabetes mellitus requiring medication, at least one other prior MI, evidence of multivessel coronary artery disease, or creatinine clearance <60 mL/min. Patients could be randomized regardless of their prior ADP receptor blocker therapy or a lapse in therapy. Patients requiring or who were expected to require renal dialysis during the study were excluded. Patients with any previous intracranial hemorrhage, gastrointestinal bleeding within the past 6 months, or with known bleeding diathesis or coagulation disorder were excluded. Patients taking anticoagulants were excluded from participating and patients who developed an indication for anticoagulation during the trial were discontinued from study drug. A small number of patients with a history of stroke were included. Based on information external to PEGASUS, 102 patients with a history of stroke (90 of whom received study drug) were terminated early and no further such patients were enrolled.

Patients were treated for at least 12 months and up to 48 months with a median follow up time of 33 months.

Patients were predominantly male (76%) Caucasian (87%) with a mean age of 65 years, and 99.8% of patients received prior aspirin therapy.

The Kaplan-Meier curve (Figure 13) shows time to first occurrence of the primary composite endpoint of CV death, non-fatal MI or non-fatal stroke.

Figure 13 – Time to First Occurrence of CV death, MI or Stroke (PEGASUS)

Ti = Ticagrelor BID, CI = Confidence interval; HR = Hazard ratio; KM = Kaplan-Meier; N = Number of patients.

Both the 60 mg and 90 mg regimens of BRILINTA in combination with aspirin were superior to aspirin alone in reducing the incidence of CV death, MI or stroke. The absolute risk reductions for BRILINTA plus aspirin vs. aspirin alone were 1.27% and 1.19% for the 60 and 90 mg regimens, respectively. Although the efficacy profiles of the two regimens were similar, the lower dose had lower risks of bleeding and dyspnea.

Table 8 shows the results for the 60 mg plus aspirin regimen vs. aspirin alone.

Table 8 - Incidences of the primary composite endpoint, primary composite endpoint components, and secondary endpoints (PEGASUS)
 | BRILINTA [60 mg BID] N=7045 | Placebo N=7067 | HR (95% CI) | p-value
 | Events / 1000 patient years | Events / 1000 patient years | HR (95% CI) | p-value
Time to first CV death, MI, or stroke [Primary composite endpoint] | 26 | 31 | 0.84 (0.74, 0.95) | 0.0043
CV Death [Secondary endpoints] [The event rate for the components CV death, MI and stroke are calculated from the actual number of first events for each component.] | 9 | 11 | 0.83 (0.68, 1.01)
Myocardial infarction | 15 | 18 | 0.84 (0.72, 0.98)
Stroke | 5 | 7 | 0.75 (0.57, 0.98)
All-cause mortality | 16 | 18 | 0.89 (0.76, 1.04)
CI = Confidence interval; CV = Cardiovascular; HR = Hazard ratio; MI = Myocardial infarction; N = Number of patients.

In PEGASUS, the relative risk reduction (RRR) for the composite endpoint from 1 to 360 days (17% RRR) and from 361 days and onwards (16% RRR) were similar.

The treatment effect of BRILINTA 60 mg over aspirin appeared similar across most pre-defined subgroups, see Figure 14.

Figure 14 – Subgroup analyses of ticagrelor 60 mg (PEGASUS)

Note: The figure above presents effects in various subgroups all of which are baseline characteristics and most of which were pre-specified. The 95% confidence limits that are shown do not take into account how many comparisons were made, nor do they reflect the effect of a particular factor after adjustment for all other factors. Apparent homogeneity or heterogeneity among groups should not be over-interpreted.

14.2 Coronary Artery Disease but No Prior Stroke or Myocardial Infarction

THEMIS

The THEMIS study (NCT01991795) was a double-blind, parallel group, study in which 19,220 patients with CAD and Type 2 Diabetes Mellitus (T2DM) but no history of MI or stroke were randomized to twice daily BRILINTA or placebo, on a background of 75-150 mg of aspirin. The primary endpoint was the composite of first occurrence of CV death, MI, and stroke. CV death, MI, ischemic stroke, and all-cause death were assessed as secondary endpoints.

Patients were eligible to participate if they were ≥ 50 years old with CAD, defined as a history of PCI or CABG, or angiographic evidence of ≥ 50% lumen stenosis of at least 1 coronary artery and T2DM treated for at least 6 months with glucose-lowering medication. Patients with previous intracerebral hemorrhage, gastrointestinal bleeding within the past 6 months, known bleeding diathesis, and coagulation disorder were excluded. Patients taking anticoagulants or ADP receptor antagonists were excluded from participating, and patients who developed an indication for those medications during the trial were discontinued from study drug.

Patients were treated for a median of 33 months and up to 58 months.

Patients were predominantly male (69%) with a mean age of 66 years. At baseline, 80% had a history of coronary artery revascularization; 58% had undergone PCI, 29% had undergone a CABG and 7% had undergone both. The proportion of patients studied in the US was 12%. Patients in THEMIS had established CAD and other risk factors that put them at higher cardiovascular risk.

BRILINTA was superior to placebo in reducing the incidence of CV death, MI, or stroke. The effect on the composite endpoint was driven by the individual components MI and stroke; see Table 9.

Table 9 - Primary composite endpoint, primary endpoint components, and secondary endpoints (THEMIS)
 | BRILINTA N=9619 | Placebo N=9601 | HR (95% CI) | p-value
 | Events / 1000 patient years | Events / 1000 patient years | HR (95% CI) | p-value
Time to first CV death, MI, or stroke [Primary endpoint] | 24 | 27 | 0.90 (0.81, 0.99) | 0.04
CV death [The event rate for the components CV death, MI and stroke are calculated from the actual number of first events for each component.] | 12 | 11 | 1.02 (0.88, 1.18)
Myocardial infarction | 9 | 11 | 0.84 (0.71, 0.98)
Stroke | 6 | 7 | 0.82 (0.67, 0.99)
Secondary endpoints
CV death | 12 | 11 | 1.02 (0.88, 1.18)
Myocardial infarction | 9 | 11 | 0.84 (0.71, 0.98)
Ischemic stroke | 5 | 6 | 0.80 (0.64, 0.99)
All-cause death | 18 | 19 | 0.98 (0.87, 1.10)
CI = Confidence interval; CV = Cardiovascular; HR = Hazard ratio; MI = Myocardial infarction.

The Kaplan-Meier curve (Figure 15) shows time to first occurrence of the primary composite endpoint of CV death, MI, or stroke.

Figure 15 - Time to First Occurrence of CV death, MI or Stroke (THEMIS)

T = Ticagrelor; P = Placebo; N = Number of patients.

The treatment effect of BRILINTA appeared similar across patient subgroups, see Figure 16.

Figure 16 – Subgroup analyses of ticagrelor (THEMIS)

Note: The figure above presents effects in various subgroups all of which are baseline characteristics. The 95% confidence limits that are shown do not take into account how many comparisons were made, nor do they reflect the effect of a particular factor after adjustment for all other factors. Apparent homogeneity or heterogeneity among groups should not be over-interpreted.

14.3 Acute Ischemic Stroke or Transient Ischemic Attack (TIA)

THALES

The THALES study (NCT03354429) was a 11,016-patient, randomized, double-blind, parallel-group study of BRILINTA 90 mg twice daily versus placebo in patients with acute ischemic stroke or transient ischemic attack (TIA). The primary endpoint was the first occurrence of the composite of stroke and death up to 30 days. Ischemic stroke was assessed as one of the secondary endpoints.

Patients were eligible to participate if they were ≥40 years old, with non-cardioembolic acute ischemic stroke (NIHSS score ≤5) or high-risk TIA (defined as ABCD2 score ≥6 or ipsilateral atherosclerotic stenosis ≥50% in the internal carotid or an intracranial artery). Patients who received thrombolysis or thrombectomy within 24 hours prior to randomization were not eligible.

Patients were randomized within 24 hours of onset of an acute ischemic stroke or TIA to receive 30 days of either BRILINTA (90 mg twice daily, with an initial loading dose of 180 mg) or placebo, on a background of aspirin initially 300-325 mg then 75-100 mg daily. The median treatment duration was 31 days.

BRILINTA was superior to placebo in reducing the rate of the primary endpoint (composite of stroke and death), corresponding to a relative risk reduction (RRR) of 17% and an absolute risk reduction (ARR) of 1.1% (Table 10). The effect was driven primarily by a significant reduction in the stroke component of the primary endpoint (19% RRR, 1.1% ARR).

Table 10 - Incidences of the primary composite endpoint, primary composite endpoint components, and secondary endpoint (THALES)
 | BRILINTA; N=5523 |  | Placebo; N=5493 |  | HR (95% CI) | p-value
 | n (patients with event) | KM% | n (patients with event) |  | HR (95% CI) | KM%
Time to first Stroke or Death | 303 | 5.4% | 362 | 6.5% | 0.83 (0.71, 0.96) | 0.015
Time to first Stroke [The number of patients with the event of interest. In the time to first stroke, patients who died are censored at the time of death.] | 284 | 5.1% | 347 | 6.3% | 0.81 (0.69, 0.95)
Time to Death | 36 | 0.6% | 27 | 0.5% | 1.33 (0.81, 2.19)
Secondary Endpoint
Time to first Ischemic Stroke | 276 | 5.0% | 345 | 6.2% | 0.79 (0.68, 0.93) | 0.004
CI = Confidence interval; HR = Hazard ratio; KM = Kaplan-Meier percentage calculated at 30 days; N = Number of patients

The Kaplan-Meier curve (Figure 17) shows the time to first occurrence of the primary composite endpoint of stroke and death.

Figure 17 – Time to First Occurrence of Stroke or Death (THALES)

KM%: Kaplan-Meier percentage evaluated at Day 30; T=Ticagrelor; P=placebo; N=Number of patients

BRILINTA’s treatment effect on stroke and on death accrued over the first 10 days and was sustained at 30 days. Although not studied, this suggests that shorter treatment could result in similar benefit and reduced bleeding risk.

The treatment effect of BRILINTA was generally consistent across pre-defined subgroups (Figure 18).

Figure 18 - Subgroup analyses of ticagrelor 90 mg (THALES)

Note: The figure above presents effects in various subgroups all of which are baseline characteristics and were pre-specified. The 95% confidence limits that are shown do not take into account how many comparisons were made, nor do they reflect the effect of a particular factor after adjustment for all other factors. Apparent homogeneity or heterogeneity among groups should not be over-interpreted.

At Day 30, there was an absolute reduction of 1.2% (95% CI: -2.1%, -0.3%) in the incidence of non-hemorrhagic stroke and death (excluding fatal bleed) favoring ticagrelor (294 events: 5.3%) over placebo (359 events: 6.5%) in the intention-to-treat population. In the same population, there was an absolute increase of 0.4% (95% CI: 0.2%, 0.6%) in the incidence of GUSTO severe bleeding unfavorable to ticagrelor arm (28 events: 0.5%) compared to the placebo arm (7 events: 0.1%).

16 HOW SUPPLIED/STORAGE AND HANDLING

BRILINTA (ticagrelor) 90 mg is supplied as a round, biconvex, yellow, film-coated tablet with a “90” above “T” on one side:

Overbagged with 10 film-coated tablets per bag, NDC 55154-9618-0

Bottles of approximately 1440 film-coated tablets, NDC 55154-9618-8

OVERBAG - WARNING: This Unit Dose package is not child resistant and is Intended for Institutional Use Only. Keep this and all drugs out of the reach of children.

Storage and Handling

Store at 25°C (77°F); excursions permitted to 15 to 30°C (59 to 86°F) [see USP controlled room temperature].

17 PATIENT COUNSELING INFORMATION

Advise the patient to read the FDA-approved patient labeling (Medication Guide).

Advise patients daily doses of aspirin should not exceed 100 mg and to avoid taking any other medications that contain aspirin.

Advise patients that they:

- Will bleed and bruise more easily
- Will take longer than usual to stop bleeding
- Should report any unanticipated, prolonged or excessive bleeding, or blood in their stool or urine.

Advise patients to contact their doctor if they experience unexpected shortness of breath, especially if severe.

Advise patients to inform physicians and dentists that they are taking BRILINTA before any surgery or dental procedure.

Advise women that breastfeeding is not recommended during treatment with BRILINTA [see Use in Specific Populations (8.2)].

BRILINTA® is a trademark of the AstraZeneca group of companies.

Distributed by: AstraZeneca Pharmaceuticals LP, Wilmington, DE 19850

© AstraZeneca 2024

Distributed By:

Cardinal Health

Dublin, OH 43017

L50533760825

ER7198S Rev. B

MEDICATION GUIDE

BRILINTA® (brih-LIN-tah)

(ticagrelor) Tablets

What is the most important information I should know about BRILINTA?

BRILINTA is used to lower your chance of having, or dying from, a heart attack or stroke. BRILINTA (and similar drugs) can cause bleeding that can be serious and sometimes lead to death. In cases of serious bleeding, such as internal bleeding, the bleeding may result in the need for blood transfusions or surgery. While you take BRILINTA:

- you may bruise and bleed more easily
- you are more likely to have nose bleeds
- it will take longer than usual for any bleeding to stop

Call your healthcare provider right away, if you have any of these signs or symptoms of bleeding while taking BRILINTA:

- bleeding that is severe or that you cannot control
- pink, red or brown urine
- vomiting blood or your vomit looks like “coffee grounds”
- red or black stools (looks like tar)
- coughing up blood or blood clots

Do not stop taking BRILINTA without talking to the healthcare provider who prescribes it for you. People who are treated with a stent, and stop taking BRILINTA too soon, have a higher risk of getting a blood clot in the stent, having a heart attack, or dying. If you stop BRILINTA because of bleeding, or for other reasons, your risk of a heart attack or stroke may increase.

Your healthcare provider may instruct you to stop taking BRILINTA 5 days before surgery. This will help to decrease your risk of bleeding with your surgery or procedure. Your healthcare provider should tell you when to start taking BRILINTA again, as soon as possible after surgery.

Taking BRILINTA with aspirin

BRILINTA is taken with aspirin, unless your healthcare provider specifically tells you otherwise. Talk to your healthcare provider about the dose of aspirin that you should take with BRILINTA. In most cases, you should not take a dose of aspirin higher than 100 mg daily. Do not take doses of aspirin higher than what your healthcare provider tells you to take. Tell your healthcare provider if you take other medicines that contain aspirin, and do not take new over-the-counter medicines with aspirin in them.

What is BRILINTA?

BRILINTA is a prescription medicine used to:

- decrease your risk of death, heart attack, and stroke in people with a blockage of blood flow to the heart (acute coronary syndrome or ACS) or a history of a heart attack. BRILINTA can also decrease your risk of blood clots in your stent in people who have received stents for the treatment of ACS.
- decrease your risk of a first heart attack or stroke in people who have a condition where the blood flow to the heart is decreased (coronary artery disease or CAD) who are at high risk for having a heart attack or stroke.
- decrease your risk of stroke in people who are having a stroke (acute ischemic stroke) or mini-stroke (transient ischemic attack or TIA).

It is not known if BRILINTA is safe and effective in children.

Do not take BRILINTA if you:

- have a history of bleeding in the brain
- are bleeding now
- are allergic to ticagrelor or any of the ingredients in BRILINTA. See the end of this Medication Guide for a complete list of ingredients in BRILINTA.

Before taking BRILINTA, tell your healthcare provider about all of your medical conditions, if you:

- have had bleeding problems in the past
- have had any recent serious injury or surgery
- plan to have surgery or a dental procedure. See “What is the most important information I should know about BRILINTA?”
- have a history of stomach ulcers or colon polyps
- have lung problems, such as COPD or asthma
- have liver problems
- have a history of stroke
- are pregnant or plan to become pregnant. It is not known if BRILINTA will harm your unborn baby. You and your healthcare provider should decide if you will take BRILINTA.
- are breastfeeding or plan to breastfeed. It is not known if BRILINTA passes into your breast milk. You should not breastfeed during treatment with BRILINTA. Talk to your healthcare provider about the best way to feed your baby during treatment with BRILINTA.

Tell all of your healthcare providers and dentists that you are taking BRILINTA. They should talk to the healthcare provider who prescribed BRILINTA for you before you have any surgery or procedure.

Tell your healthcare provider about all the medicines you take, including prescription and over-the-counter medicines, vitamins, and herbal supplements. BRILINTA may affect the way other medicines work, and other medicines may affect how BRILINTA works. Certain medicines may increase your risk of bleeding.

Know the medicines you take. Keep a list of them to show your healthcare provider and pharmacist when you get a new medicine.

How should I take BRILINTA?

- Take BRILINTA exactly as prescribed by your healthcare provider.
- Your healthcare provider will tell you how many BRILINTA tablets to take and when to take them.
- Take BRILINTA with aspirin, unless your healthcare provider specifically tells you otherwise. See “What is the most important information I should know about BRILINTA?”
- You may take BRILINTA with or without food.
- Take BRILINTA two times each day, around the same times each day.
- If you miss your scheduled dose of BRILINTA, take your next dose at its scheduled time. Do not take 2 doses at the same time unless your healthcare provider tells you to.
- If you take too much BRILINTA, call your healthcare provider or local poison control center or go to the nearest emergency room right away.
If you are unable to swallow the tablet(s) whole, you may crush the BRILINTA tablet(s) and mix it with water. Drink all the water right away. Refill the glass with water, stir, and drink all the water.
BRILINTA may also be given through certain nasogastric (NG) tubes. Ask your healthcare provider for instructions on how to take BRILINTA through a NG tube.

What are the possible side effects of BRILINTA?

BRILINTA can cause serious side effects, including:

- See “What is the most important information I should know about BRILINTA?”
- Shortness of breath. Tell your healthcare provider if you have new, worsening or unexpected shortness of breath when you are at rest, at night, or when you are doing any activity.
Slow or irregular heartbeat.
- Irregular breathing. Tell your healthcare provider if you develop irregular breathing patterns when asleep or awake such as speeding up, slowing down or short pauses in breathing. Your healthcare provider will decide if you need further evaluation.

These are not all of the possible side effects of BRILINTA.

Call your doctor for medical advice about side effects. You may report side effects to FDA at 1-800-FDA-1088.

How should I store BRILINTA?

- Store BRILINTA at room temperature between 68°F to 77°F (20°C to 25°C).

Keep BRILINTA and all medicines out of the reach of children.

General information about the safe and effective use of BRILINTA.

Medicines are sometimes prescribed for purposes other than those listed in a Medication Guide. Do not use BRILINTA for a condition for which it was not prescribed. Do not give BRILINTA to other people, even if they have the same symptoms you have. It may harm them. You can ask your pharmacist or healthcare provider for information about BRILINTA that is written for health professionals.

What are the ingredients in BRILINTA?

Active ingredient: ticagrelor

90 mg tablets:
Inactive ingredients: mannitol, dibasic calcium phosphate, sodium starch glycolate, hydroxypropyl cellulose, magnesium stearate, hydroxypropyl methylcellulose, titanium dioxide, talc, polyethylene glycol 400, and ferric oxide yellow.

60 mg tablets:
Inactive ingredients: mannitol, dibasic calcium phosphate, sodium starch glycolate, hydroxypropyl cellulose, magnesium stearate, hydroxypropyl methylcellulose, titanium dioxide, polyethylene glycol 400, ferric oxide black and ferric oxide red.

Distributed by: AstraZeneca Pharmaceuticals LP, Wilmington, DE 19850

For more information call 1-800-236-9933 or go to www.Brilinta.com.

Distributed By:

Cardinal Health

Dublin, OH 43017

L50533760825

ER7198S Rev. B

This Medication Guide has been approved by the U.S. Food and Drug Administration. Revised: 03/2024

Package/Label Display Panel

NDC 55154-9618-0

BRILINTA® TABLETS 90 mg

Ticagrelor

10 TABLETS

Package/Label Display Panel

Contains Approximately

1440 Tablets

BRILINTA®

(ticagrelor tablets)

90 mg

Each tablet contains:

90 mg ticagrelor.

Rx Only

WARNING: Keep out of reach of

children.